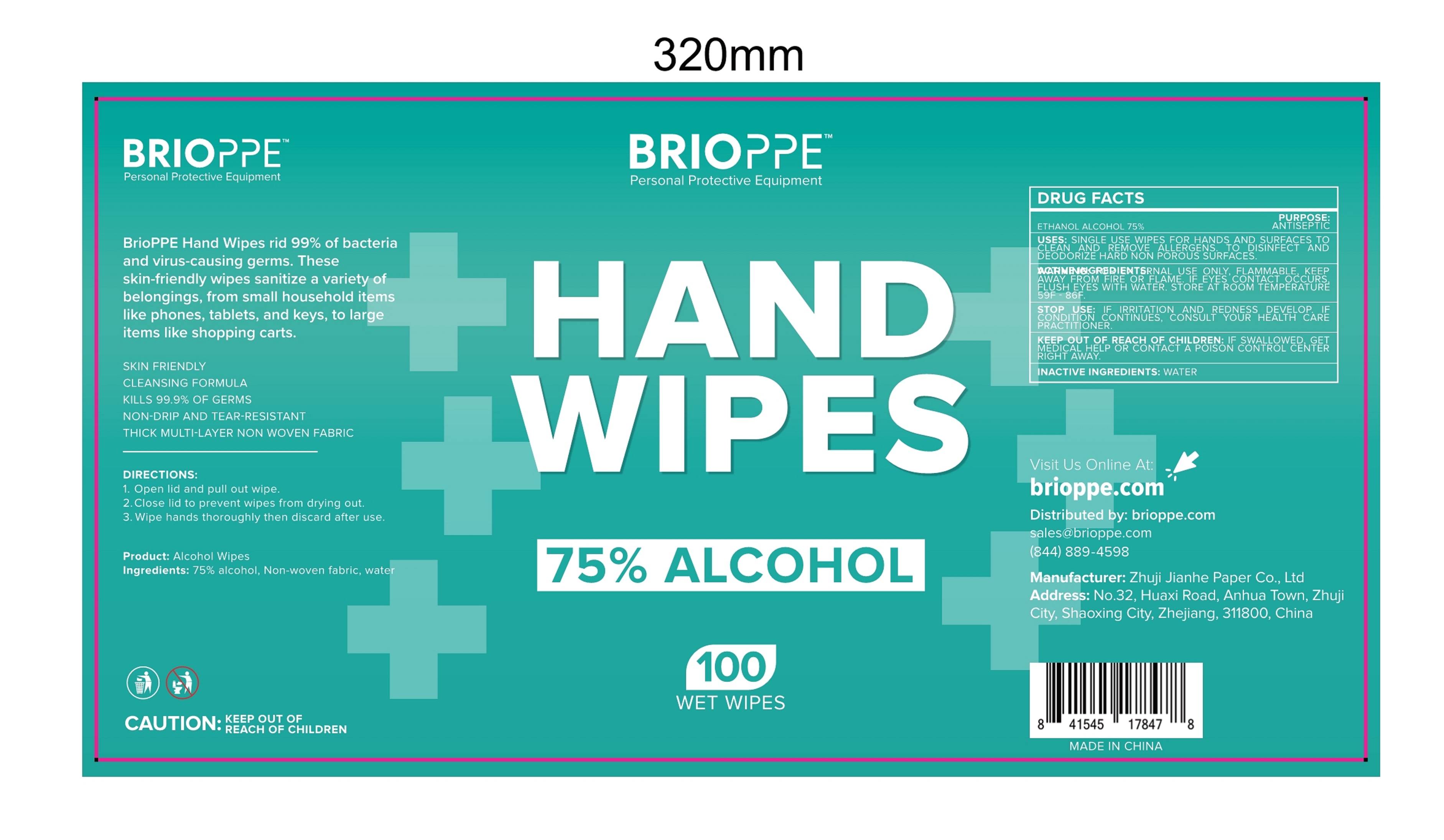 DRUG LABEL: ALCOHOL WIPES
NDC: 80313-100 | Form: CLOTH
Manufacturer: Brio Water Technology, Inc.
Category: otc | Type: HUMAN OTC DRUG LABEL
Date: 20201009

ACTIVE INGREDIENTS: ALCOHOL 4.9 mL/1 1
INACTIVE INGREDIENTS: WATER

80313-100 100 wet wipes jianhe

Active Ingredient(s)

Alcohol 75% v/v. Purpose: Antiseptic

Purpose

Antiseptic, WET WIPES

Use

SINGLE USE WIPES FOR HANDS AND SURFACES TO CLEAN AND REMOVE ALLERGENS. TO DISINFECT AND DEODORIZE HARD NON POROUS SURFACES.

Do not use

- in children less than 2 months of age
- on open skin wounds

Warnings

FOR EXTERNAL USE ONLY, FLAMMABLE, KEEP AWAY FROM FIRE OR FLAME. IF EYES CONTACT OCCURS, FLUSH EYES WITH WATER. STORE AT ROOM TEMPERATURE 59F-86F.

When using this product keep out of eyes, ears, and mouth. In case of contact with eyes, rinse eyes thoroughly with water.
Stop use and ask a doctor if irritation or rash occurs. These may be signs of a serious condition.
Keep out of reach of children. If swallowed, get medical help or contact a Poison Control Center right away.

Stop use and ask a doctor if irritation and redness develop. If condition continues, consult your health care practitioner.

Keep out of reach of children. If swallowed, get medical help or contact a Poison Control Center right away.

Directions

1.Open lid and pull out wipe.

2.Close lid to prevent wipes from drying out.

3.Wipe hands thoroughly then discard after use.

Other information

- Store between 59-86F

Inactive ingredients

water

Package Label - Principal Display Panel

100 WET WIPES NDC: 80313-100-01